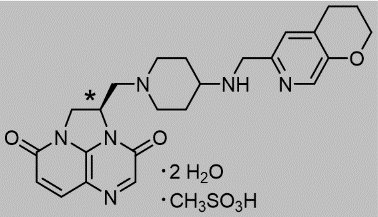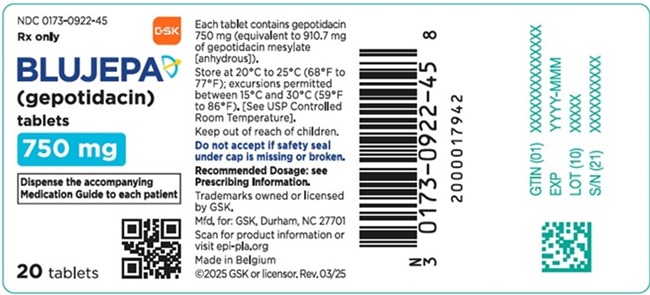 DRUG LABEL: Blujepa
NDC: 0173-0922 | Form: TABLET, FILM COATED
Manufacturer: GlaxoSmithKline LLC
Category: prescription | Type: HUMAN PRESCRIPTION DRUG LABEL
Date: 20260210

ACTIVE INGREDIENTS: GEPOTIDACIN MESYLATE 750 mg/1 1
INACTIVE INGREDIENTS: SILICON DIOXIDE; CROSCARMELLOSE SODIUM; MAGNESIUM STEARATE; MICROCRYSTALLINE CELLULOSE; POLYVINYL ALCOHOL, UNSPECIFIED; POLYETHYLENE GLYCOL, UNSPECIFIED; TALC; TITANIUM DIOXIDE; FERRIC OXIDE YELLOW

HIGHLIGHTS OF PRESCRIBING INFORMATION

These highlights do not include all the information needed to use BLUJEPA safely and effectively. See full prescribing information for BLUJEPA.
BLUJEPA (gepotidacin) tablets, for oral use
Initial U.S. Approval: 2025

RECENT MAJOR CHANGES

Indications and Usage (1.2) | 12/2025
Dosage and Administration (2.2) | 12/2025
Warnings and Precautions (5.1) | 12/2025

1 INDICATIONS AND USAGE

BLUJEPA is a triazaacenaphthylene bacterial type II topoisomerase inhibitor indicated for the treatment of the following infections caused by susceptible microorganisms:

- Uncomplicated urinary tract infections (uUTI) in female adult and pediatric patients 12 years of age and older weighing at least 40 kilograms (kg). (1.1)
- Uncomplicated urogenital gonorrhea in adult and pediatric patients 12 years of age and older weighing at least 45 kilograms who have limited or no alternative treatment options. Approval of this indication is based on limited clinical safety data for this indication. (1.2, 6.1)

Usage to Reduce Development of Drug-Resistant Bacteria

To reduce the development of drug-resistant bacteria and maintain the effectiveness of BLUJEPA and other antibacterial drugs, BLUJEPA should be used only to treat infections that are proven or strongly suspected to be caused by bacteria. (1.3)

2 DOSAGE AND ADMINISTRATION

- uUTI: The recommended dosage of BLUJEPA is 1,500 mg (two 750 mg tablets) taken orally, twice daily (approximately 12 hours apart), for 5 days. (2.1)
- Uncomplicated Urogenital Gonorrhea: The recommended dosage of BLUJEPA is 3,000 mg (four 750 mg tablets) taken orally, followed by a second dose of 3,000 mg (four 750 mg tablets) approximately 12 hours later. (2.2)
- Administer BLUJEPA tablets after a meal to reduce the possibility of gastrointestinal intolerance. (2.3)

3 DOSAGE FORMS AND STRENGTHS

Tablets: 750 mg of gepotidacin. (3)

4 CONTRAINDICATIONS

A history of severe hypersensitivity to BLUJEPA. (4)

5 WARNINGS AND PRECAUTIONS

- QTc Prolongation:
- Avoid use of BLUJEPA in patients with a history of QTc prolongation, or with relevant pre‑existing cardiac disease, or in patients receiving drugs that prolong the QTc interval. (5.1)
- Due to an increase in gepotidacin exposure and the risk of QTc interval prolongation, avoid use of BLUJEPA in patients who have any of the following risk factors: (5.1, 7.1, 8.6, 8.7)
- Concomitant use of strong CYP3A4 inhibitors
- Severe renal impairment (estimated glomerular filtration rate [eGFR] <30 mL/min)
- Severe hepatic impairment (Child-Pugh Class C)
- Additionally, avoid BLUJEPA in uncomplicated urogenital gonorrhea patients, who have any of the following risk factors for increased gepotidacin exposure: (5.1, 7.1, 8.6, 8.7)
- Concomitant use of moderate CYP3A4 inhibitors
- Two or more of the following risk factors: Body weight between 45 kilograms and 60 kilograms, Moderate renal impairment (eGFR 30 to 59 mL/min), Moderate hepatic impairment (Child-Pugh Class B)
- Acetylcholinesterase Inhibition: Dysarthria and other adverse reactions have been reported in patients receiving BLUJEPA. Monitor patients with underlying medical conditions that may be exacerbated by acetylcholinesterase inhibition and patients receiving succinylcholine‑type neuromuscular blocking agents, systemic anticholinergic medications, or non‑depolarizing neuromuscular blocking agents. (5.2)
- Hypersensitivity Reactions: Hypersensitivity reactions, including anaphylaxis, have been reported in patients receiving BLUJEPA. If an allergic reaction to BLUJEPA occurs, discontinue the drug and institute appropriate supportive measures. (5.3)
- Clostridioides difficile Infection (CDI): CDI has been reported with nearly all systemic antibacterial agents, including BLUJEPA. Evaluate patients who develop diarrhea. (5.4)

6 ADVERSE REACTIONS

- uUTI: The most common adverse reactions occurring in ≥1% of patients are diarrhea, nausea, abdominal pain, flatulence, headache, soft feces, dizziness, vomiting, and vulvovaginal candidiasis. (6.1)
- Uncomplicated Urogenital Gonorrhea: The most common adverse reactions occurring in ≥2% of patients are diarrhea, nausea, abdominal pain, vomiting, flatulence, dizziness, soft feces, headache, fatigue, and hyperhidrosis. (6.1)

To report SUSPECTED ADVERSE REACTIONS, contact GlaxoSmithKline at 1-888-825-5249 or FDA at 1-800-FDA-1088 or www.fda.gov/medwatch.

7 DRUG INTERACTIONS

- CYP3A4 Inhibitors: Increase gepotidacin exposure. (7.1)
- Strong CYP3A4 inhibitors: Avoid concomitant use of BLUJEPA with strong CYP3A4 inhibitors. (5.1, 7.1)
- Moderate CYP3A4 inhibitors: Avoid concomitant use of BLUJEPA with moderate CYP3A4 inhibitors in patients with uncomplicated urogenital gonorrhea. (5.1, 7.1)
- CYP3A4 Inducers: Decrease gepotidacin exposure. (7.1)
- For uUTI: Avoid concomitant use of BLUJEPA with strong CYP3A4 inducers. (7.1)
- For uncomplicated urogenital gonorrhea: Avoid concomitant use of BLUJEPA with strong and moderate CYP3A4 inducers. (7.1)
- CYP3A4 Substrates: Avoid concomitant use of BLUJEPA with drugs that are extensively metabolized by CYP3A4 where minimal concentration changes may lead to serious adverse reactions. (7.2)
- Digoxin: Due to an increase in digoxin exposures, consider monitoring digoxin serum concentration, as appropriate, with concomitant administration of BLUJEPA. (7.2)

8 USE IN SPECIFIC POPULATIONS

- Renal Impairment: Avoid use of BLUJEPA in patients with severe renal impairment with eGFR <30 mL/min, including those receiving dialysis. (8.6)
- Hepatic Impairment: Avoid use of BLUJEPA in patients with severe hepatic impairment (Child-Pugh Class C). (8.7)

FULL PRESCRIBING INFORMATION

1 INDICATIONS AND USAGE

1.1 Treatment of Uncomplicated Urinary Tract Infections

BLUJEPA is indicated in female adult and pediatric patients 12 years of age and older weighing at least 40 kilograms (kg) for the treatment of uncomplicated urinary tract infections (uUTI) caused by the following susceptible microorganisms: Escherichia coli, Klebsiella pneumoniae, Citrobacter freundii complex, Staphylococcus saprophyticus, and Enterococcus faecalis.

1.2 Treatment of Uncomplicated Urogenital Gonorrhea

BLUJEPA is indicated in adult and pediatric patients 12 years of age and older weighing at least 45 kilograms (kg) who have limited or no alternative options for the treatment of uncomplicated urogenital gonorrhea caused by susceptible strains of Neisseria gonorrhoeae. Approval of this indication is based on limited clinical safety data for BLUJEPA [see Adverse Reactions (6.1)].

1.3 Usage to Reduce Development of Drug-Resistant Bacteria

To reduce the development of drug-resistant bacteria and maintain the effectiveness of BLUJEPA and other antibacterial drugs, BLUJEPA should be used only to treat infections that are proven or strongly suspected to be caused by susceptible bacteria. When culture and susceptibility information are available, they should be considered in selecting or modifying antibacterial therapy. In the absence of such data, local epidemiology and susceptibility patterns may contribute to the empiric selection of therapy.

2 DOSAGE AND ADMINISTRATION

2.1 Recommended Dosage for Female Adult and Pediatric Patients 12 Years of Age and Older Weighing at Least 40 kg for Uncomplicated UTI

The recommended dosage of BLUJEPA is 1,500 mg (two 750 mg tablets) taken orally, twice daily (approximately 12 hours apart) for 5 days in female adult and pediatric patients 12 years of age and older with uncomplicated uUTI [see Dosage and Administration (2.3)].

2.2 Recommended Dosage for Adult and Pediatric Patients 12 Years of Age and Older Weighing at Least 45 kg for Uncomplicated Urogenital Gonorrhea

The recommended dose of BLUJEPA is 3,000 mg (four 750 mg tablets) taken orally, followed by a second dose of 3,000 mg (four 750 mg tablets) approximately 12 hours later in adult and pediatric patients 12 years of age and older weighing at least 45 kg with uncomplicated urogenital gonorrhea [see Dosage and Administration (2.3)].

Do not increase the dose, extend the duration of treatment, or reduce the interval between doses due to the risk of QTc interval prolongation [see Warnings and Precautions (5.1)].

2.3 Important Administration Instructions

Administer BLUJEPA tablets after a meal to reduce the possibility of gastrointestinal intolerance [see Adverse Reactions (6.1), Clinical Pharmacology (12.3)].

2.4 Recommendations Regarding Missed Dose(s)

If a dose is missed, instruct patients to take the missed dose as soon as possible. For uUTI, do not double the dose to make up for a missed dose.

3 DOSAGE FORMS AND STRENGTHS

Each film coated tablet of BLUJEPA contains 750 mg of gepotidacin. BLUJEPA tablets are yellow, capsule shaped, and debossed with “GS GU3” on one side and plain on the other side.

4 CONTRAINDICATIONS

BLUJEPA is contraindicated in patients with a history of severe hypersensitivity to BLUJEPA [see Warnings and Precautions (5.3), Adverse Reactions (6.1)].

5 WARNINGS AND PRECAUTIONS

5.1 QTc Prolongation

A dose and concentration-dependent prolongation of the QTc interval has been observed with BLUJEPA [see Clinical Pharmacology (12.2)].

Avoid BLUJEPA in patients with a history of QTc interval prolongation or those with relevant pre‑existing cardiac disease, patients taking antiarrhythmic agents, or other medications that may potentially prolong the QTc interval [see Drug Interactions (7.4)].

Due to an increase in gepotidacin exposure (Cmax), and the risk of QTc interval prolongation, avoid BLUJEPA in patients who have any of the following risk factors [see Drug Interactions (7.1), Use in Specific Populations (8.6, 8.7)]:

- Concomitant use of strong CYP3A4 inhibitors
- Severe renal impairment (estimated glomerular filtration rate [eGFR] <30 mL/min)
- Severe hepatic impairment (Child-Pugh Class C)

Additionally, avoid BLUJEPA in uncomplicated urogenital gonorrhea patients who also have any of the following risk factors for increased gepotidacin exposure [see Drug Interactions (7.1), Use in Specific Populations (8.6, 8.7)]:

- Concomitant use of moderate CYP3A4 inhibitors
- Two or more of the following risk factors:
  - Body weight between 45 kg and 60 kg
  - Moderate renal impairment (eGFR 30 to 59 mL/min)
  - Moderate hepatic impairment (Child‑Pugh Class B)

If administration of BLUJEPA cannot be avoided in these patients, monitor and correct serum electrolyte abnormalities and collect an ECG prior to administration and during treatment, as clinically indicated.

5.2 Acetylcholinesterase Inhibition

BLUJEPA is a reversible acetylcholinesterase inhibitor in in vitro laboratory studies. Adverse reactions including dysarthria, syncope, presyncope, muscle spasms, diarrhea, nausea, vomiting, abdominal pain, hypersalivation, and hyperhidrosis which are potentially attributed to acetylcholinesterase inhibition, have been observed in clinical trials [see Adverse Reactions (6.1)]. Increased cholinergic effects can be associated with severe adverse reactions including atrioventricular block, bradycardia, bronchospasm, and seizures/convulsions. Monitor patients with medical conditions that may be exacerbated by acetylcholinesterase inhibition.

BLUJEPA, as an acetylcholinesterase inhibitor, may exaggerate the neuromuscular effects of succinylcholine‑type muscle relaxation during anesthesia. BLUJEPA may exaggerate the effects of other acetylcholinesterase inhibitors. Monitor patients for exaggerated neuromuscular blockade or excessive cholinergic effects.

Because BLUJEPA may antagonize the effects of systemic anticholinergic medications or non‑depolarizing neuromuscular blocking agents, monitor patients if BLUJEPA is concomitantly administered with these medications [see Drug Interactions (7.3)].

5.3 Hypersensitivity Reactions

Hypersensitivity reactions, including anaphylaxis, have been reported in patients receiving BLUJEPA [see Adverse Reactions (6.1)]. BLUJEPA is contraindicated in patients with a history of severe hypersensitivity to BLUJEPA [see Contraindications (4)]. Before therapy with BLUJEPA is instituted, carefully inquire about previous hypersensitivity reactions to BLUJEPA. If an allergic reaction to BLUJEPA occurs, discontinue the drug and institute appropriate supportive measures.

5.4 Clostridioides difficile Infection

Clostridioides difficile (C. difficile) infection (CDI) has been reported for nearly all systemic antibacterial agents, including BLUJEPA, and may range in severity from mild diarrhea to fatal colitis [see Adverse Reactions (6)]. Treatment with antibacterial agents alters the normal flora of the colon leading to overgrowth of C. difficile.

C. difficile produces toxins A and B which contribute to the development of CDI. Hypertoxin producing isolates of C. difficile cause increased morbidity and mortality, as these infections can be refractory to antimicrobial therapy and may require colectomy. CDI must be considered in all patients who present with diarrhea following antibacterial drug use. Careful medical history is necessary since CDI has been reported to occur over 2 months after the administration of antibacterial agents.

If CDI is suspected or confirmed, ongoing antibacterial drug use not directed against C. difficile may need to be discontinued. Appropriate fluid and electrolyte management, protein supplementation, antibacterial drug treatment of C. difficile, and surgical evaluation should be instituted as clinically indicated.

5.5 Development of Drug-Resistant Bacteria

Prescribing BLUJEPA in the absence of a proven or strongly suspected bacterial infection is unlikely to provide benefit to the patient and increases the risk of the development of drug‑resistant bacteria [see Indications and Usage (1.3)].

6 ADVERSE REACTIONS

The following adverse reactions are discussed in greater detail in other sections of the labeling:

- QTc Prolongation [see Warnings and Precautions (5.1)].
- Acetylcholinesterase Inhibition [see Warnings and Precautions (5.2)].
- Hypersensitivity Reactions [see Warnings and Precautions (5.3)].
- Clostridioides difficile Infection [see Warnings and Precautions (5.4)].

6.1 Clinical Trials Experience

Because clinical trials are conducted under widely varying conditions, adverse reaction rates observed in the clinical trials of a drug cannot be directly compared with rates in the clinical trials of another drug and may not reflect the rates observed in practice.

Clinical Trial Experience in Patients with Uncomplicated UTI

The safety of BLUJEPA was evaluated in 2 double‑blind, active‑controlled, randomized trials in female adult and pediatric patients 12 years of age and older with uUTI (Trial 1 and Trial 2). A total of 1,570 patients were treated with BLUJEPA and 1,558 patients were treated with nitrofurantoin (pooled safety populations for BLUJEPA and nitrofurantoin, respectively). Patients received treatment for a median duration of 5 days.

In Trials 1 and 2 (pooled, intent-to-treat [ITT] population), the median age of patients treated with BLUJEPA was 49 (range 13 to 89) years; <1% were <18 years, 77% of patients were 18 to 64 years, 14% were 65 to 74 years, and 8% were ≥75 years. Patients were female (100%) and White (83%), Black or African American (7%), Asian (5%), or American Indian or Alaskan Native (4%); for ethnicity, 33% identified as Hispanic/Latino and 67% as non-Hispanic/Latino. The majority of patients were enrolled from the U.S. (55%).

Serious Adverse Reactions and Adverse Reactions Leading to Discontinuation: In the pooled trials (Trials 1 and 2), serious adverse reactions occurred in 1/1,570 (<1%) uUTI patients treated with BLUJEPA and 1/1,558 (<1%) uUTI patients treated with nitrofurantoin. The serious adverse reaction reported with BLUJEPA was dysarthria. No adverse reaction led to death in either treatment group.

In the pooled trials, adverse reactions leading to discontinuation of treatment occurred in 79/1,570 (5%) uUTI patients treated with BLUJEPA and 30/1,558 (2%) uUTI patients treated with nitrofurantoin. Adverse reactions occurring in >1% of patients leading to treatment discontinuation in patients treated with BLUJEPA included diarrhea (3%) and nausea (1%).

Common Adverse Reactions: Table 1 lists the adverse reactions occurring in ≥1% of uUTI patients receiving BLUJEPA in the pooled trials (Trials 1 and 2).

Table 1. Adverse Reactions Occurring in ≥1% of Uncomplicated Urinary Tract Infection Patients Treated with BLUJEPA (Trials 1 and 2 Pooled Data; Safety Population)
Adverse Reaction | BLUJEPA; N = 1,570; n (%) | Nitrofurantoin; N = 1,558; n (%)
Diarrhea | 258 (16) | 51 (3)
Nausea | 146 (9) | 64 (4)
Abdominal paina | 60 (4) | 34 (2)
Flatulence | 43 (3) | 8 (<1)
Headache | 38 (2) | 40 (3)
Soft feces | 37 (2) | 8 (<1)
Dizziness | 29 (2) | 19 (1)
Vomiting | 28 (2) | 10 (<1)
Vulvovaginal candidiasis | 20 (1) | 18 (1)
a Abdominal pain includes abdominal pain, abdominal pain upper, abdominal pain lower, abdominal tenderness, abdominal discomfort, and gastrointestinal pain.

Diarrhea: In Trials 1 and 2, diarrhea was reported in 258/1,570 (16%) uUTI patients receiving BLUJEPA; 11% mild, 5% moderate, and <1% severe. The diarrhea started within the first 2 days of treatment for the majority of patients and the median duration of diarrhea was 4 days.

Adverse Reactions Occurring in Less than 1% of uUTI Patients Receiving BLUJEPA in Trials 1 and 2 (Pooled):

Gastrointestinal Disorders: Abdominal distension, dyspepsia (includes epigastric discomfort, eructation)

Nervous System Disorders: Presyncope, dysarthria

Infections and Infestations: Clostridioides difficile infection

Musculoskeletal and Connective Tissue Disorders: Muscle spasms

Vascular Disorders: Hot flush

Cardiac Disorders: Tachycardia

Eye Disorders: Blurred vision

Ear and Labyrinth Disorders: Vertigo

General Disorders and Administration Site Disorders: Fatigue

Investigations: Alanine aminotransferase/aspartate aminotransferase increased

Skin and Subcutaneous Tissue: Rash, hyperhidrosis

Immune System Disorders: Hypersensitivity reactions

Select Adverse Reactions Occurring in uUTI Patients Receiving BLUJEPA in Phase 1 and 2 Clinical Studies: Gastrointestinal Disorders: Hypersalivation (with oral daily doses ranging from 100 mg to 6,000 mg, which includes not approved doses)

Clinical Trial Experience in Patients with Uncomplicated Urogenital Gonorrhea

The safety of BLUJEPA was evaluated in a randomized, active‑controlled trial (Trial 3) comparing BLUJEPA to ceftriaxone and azithromycin in adult and pediatric patients 12 years of age and older with uncomplicated urogenital gonorrhea. A total of 309 patients received at least one dose of BLUJEPA (safety population).

In Trial 3 (ITT population), the median age of patients randomized to receive BLUJEPA was 33 (range 16 to 64) years; >99% of patients were 18 to 65 years (no patients were >65 years). Overall, patients randomized to receive BLUJEPA treatment were predominately male (89%) and White (74%).

Serious Adverse Reactions and Adverse Reactions Leading to Discontinuation: No serious adverse reactions occurred in uncomplicated urogenital gonorrhea patients treated with BLUJEPA in Trial 3. Adverse reactions leading to discontinuation of treatment occurred in 3/309 (<1%) of uncomplicated urogenital gonorrhea patients treated with BLUJEPA.

Common Adverse Reactions: Table 2 lists the adverse reactions occurring in ≥2% of uncomplicated urogenital gonorrhea patients receiving BLUJEPA in Trial 3.

Table 2. Adverse Reactions Occurring in ≥2% of Uncomplicated Urogenital Gonorrhea Patients Treated with BLUJEPA (Trial 3; Safety Population)
Adverse Reaction | BLUJEPA; N = 309; n (%) | Ceftriaxone and Azithromycin; N = 313; n (%)
Diarrhea | 151 (49) | 30 (10)
Nausea | 73 (24) | 9 (3)
Abdominal paina | 25 (8) | 6 (2)
Vomiting | 20 (6) | 2 (<1)
Flatulence | 20 (6) | 1 (<1)
Dizziness | 16 (5) | 2 (<1)
Soft feces | 16 (5) | 1 (<1)
Headache | 10 (3) | 8 (3)
Fatigueb | 10 (3) | 0
Hyperhidrosis | 7 (2) | 0
a Abdominal pain includes abdominal pain, abdominal pain upper, and abdominal discomfort.
b Fatigue includes fatigue and lethargy.

Diarrhea: In Trial 3, diarrhea was reported in 151/309 (49%) uncomplicated urogenital gonorrhea patients receiving BLUJEPA (38% mild severity, 11% moderate severity). Most episodes of diarrhea started on the same day as dosing, with few diarrhea episodes after day 2. The median duration was 2 days. Discontinuation of BLUJEPA due to diarrhea was reported in 1/309 (<1%) uncomplicated urogenital gonorrhea patients.

Adverse Reactions Occurring in Less than 2% of Uncomplicated Urogenital Gonorrhea Patients Receiving BLUJEPA in Trial 3:

Skin and Subcutaneous Tissue: Rash

Cardiac Disorders: Tachycardia

Nervous System Disorders: Dysarthria, presyncope, syncope

Musculoskeletal and Connective Tissue Disorders: Muscle spasms, myalgia, arthralgia

Vascular Disorders: Hot flush

Gastrointestinal Disorders: Hypersalivation, abdominal distension

Eye Disorders: Vision blurred

Ear and Labyrinth Disorders: Vertigo

7 DRUG INTERACTIONS

7.1 Effect of Other Drugs on BLUJEPA

CYP3A4 Inhibitors

Table 3. Recommendations for Concomitant Administration of CYP3A4 Inhibitors with BLUJEPA
Indication | Moderate CYP3A4 Inhibitors | Strong CYP3A4 Inhibitors
Uncomplicated UTI | No dosage adjustment | Avoid concomitant administration of BLUJEPA with strong inhibitors of CYP3A4 due to an increase in gepotidacin exposure [see Warnings and Precautions (5.1), Clinical Pharmacology (12.3)].
Uncomplicated Urogenital Gonorrhea | Avoid concomitant administration of BLUJEPA with moderate CYP3A4 inhibitors due to an increase in gepotidacin exposure [see Warnings and Precautions (5.1), Clinical Pharmacology (12.3)]. | Avoid concomitant administration of BLUJEPA with strong inhibitors of CYP3A4 due to an increase in gepotidacin exposure [see Warnings and Precautions (5.1), Clinical Pharmacology (12.3)].

CYP3A4 Inducers

Due to decreased gepotidacin exposures, avoid coadministration of BLUJEPA with CYP3A4 inducers as follows:

- Uncomplicated urinary tract infections: Avoid concomitant use of BLUJEPA with strong CYP3A4 inducers [see Clinical Pharmacology (12.3)].
- Uncomplicated urogenital gonorrhea: Avoid concomitant use of BLUJEPA with strong and moderate CYP3A4 inducers [see Clinical Pharmacology (12.3)].

7.2 Effect of BLUJEPA on Other Drugs

CYP3A4 Substrates

Avoid concomitant administration of BLUJEPA with drugs that are extensively metabolized by CYP3A4 where minimal concentration changes may lead to serious adverse reactions [see Clinical Pharmacology (12.3)].

Digoxin

Due to an increase in digoxin exposures, consider monitoring digoxin serum concentrations, as appropriate, with concomitant administration of BLUJEPA [see Clinical Pharmacology (12.3)].

7.3 Cholinergic/Anticholinergic Drugs

As gepotidacin is an acetylcholinesterase inhibitor, there is potential for an exaggerated effect of concomitantly administered succinylcholine‑type neuromuscular blocking agents resulting in a delay in recovery of neuromuscular function. BLUJEPA may augment the effect of other acetylcholinesterase inhibitors. Monitor for exaggerated neuromuscular blockade or excessive cholinergic effects [see Warnings and Precautions (5.2)].

There is potential for an antagonistic effect with systemic anticholinergic medications or non‑depolarizing neuromuscular blocking agents. Consider the potential for this interaction if BLUJEPA is administered concomitantly with anticholinergic medications [see Warnings and Precautions (5.2)].

7.4 Drugs that Prolong the QTc Interval

Due to the increased risk of QTc prolongation, avoid concomitant administration of BLUJEPA with other medications that have the potential to prolong the QTc interval [see Warnings and Precautions (5.1)].

8 USE IN SPECIFIC POPULATIONS

8.1 Pregnancy

Pregnancy Exposure Registry

A pregnancy exposure registry will be established to monitor pregnancy outcomes in women exposed to BLUJEPA during pregnancy. Pregnant women exposed to BLUJEPA, and healthcare providers are encouraged to contact GlaxoSmithKline at 1‑888‑825‑5249.

Risk Summary

There are no available data on the use of BLUJEPA in pregnant women to evaluate for a drug‑associated risk for major birth defects, miscarriage, or other adverse maternal or fetal outcomes.

In embryo‑fetal development studies in mice and rats, decreased fetal weights and increased fetal mortality (late resorptions) were observed at exposures less than the maximum recommended human dose (MRHD). In a mouse pre- and postnatal development study, there were no adverse developmental effects at exposures approximately equal to the MRHD (see Data).

The background risk of major birth defects and miscarriage for the indicated population is unknown. All pregnancies have a background risk of birth defect, loss, or other adverse outcomes. In the U.S. general population, the estimated background risk of major birth defects and miscarriage, in clinically recognized pregnancies, is 2% to 4% and 15% to 20%, respectively.

Data

Animal Data: Gepotidacin did not cause malformations when orally administered in embryo‑fetal development studies during organogenesis. Decreased fetal weights were seen in rats dosed orally with 450 mg/kg/day or greater (less than the MRHD based on AUC extrapolated from nonpregnant rats). Decreased fetal weights and increased late fetal resorptions were seen in mice at oral doses 500 mg/kg/day or greater (less than the MRHD based on AUC extrapolated from nonpregnant mice).

In a pre- and post‑natal development study in mice given oral doses of up to 1,000 mg/kg/day (approximately equal to the MRHD), there were no gepotidacin effects on parturition, or post‑natal growth and development of the offspring.

8.2 Lactation

Risk Summary

There are no data on the presence of gepotidacin in human milk, its effects on the breastfed child, or on milk production. Based on a study in lactating mice, gepotidacin is likely transferred into milk (see Data). When a drug is present in animal milk, it is likely that the drug will be present in human milk.

The developmental and health benefits of breastfeeding should be considered along with the mother's clinical need for BLUJEPA and any potential adverse effects on the breastfed child from BLUJEPA or from the underlying maternal condition.

Data

Gepotidacin concentrations in milk have not been measured directly in animals. However, in a pre- and post‑natal development study when gepotidacin was orally administered to maternal mice during pregnancy and lactation, at all tested doses, gepotidacin was detected in the plasma of their nursing offspring (with dosing 200 mg/kg/day or greater, which was expected to result in maternal exposures as low as 0.2-times the MHRD as extrapolated from exposures in nonpregnant mice).

8.4 Pediatric Use

Uncomplicated UTI

The safety and effectiveness of BLUJEPA for the treatment of uUTI have been established for the treatment of uncomplicated UTI in female pediatric patients 12 years of age and older, weighing at least 40 kg. Use of BLUJEPA in these patients is supported by evidence from adequate and well‑controlled studies of BLUJEPA in female adult and pediatric patients 12 years of age and older with uUTI and additional pharmacokinetic data in pediatric patients (12 to <18 years of age) [see Clinical Pharmacology (12.3), Clinical Studies (14.1)]. The safety profile of BLUJEPA in female pediatric patients 12 years of age and older was similar to female adults with uUTI treated with BLUJEPA [see Adverse Reactions (6.1), Clinical Studies (14.1)].

The safety and effectiveness of BLUJEPA have not been established in pediatric patients less than 12 years of age or weighing less than 40 kg.

Uncomplicated Urogenital Gonorrhea

The safety and effectiveness of BLUJEPA for the treatment of uncomplicated urogenital gonorrhea have been established in pediatric patients 12 years of age and older weighing at least 45 kg who have limited or no alternative treatment options [see Indications and Usage (1.1)]. Use of BLUJEPA in these patients is supported by evidence from an adequate and well‑controlled study (Trial 3) in adult and pediatric patients with uncomplicated urogenital gonorrhea weighing at least 45 kg, and additional pharmacokinetic analyses showing similar drug exposure levels for pediatric patients (12 to <18 years of age) compared with adults [see Clinical Pharmacology (12.3), Clinical Studies (14.2)]. The safety profile of BLUJEPA was similar between pediatric healthy volunteers 12 to <18 years of age (n = 12) who received two 3,000 mg doses compared to adults [see Adverse Reactions (6.1)].

The safety and effectiveness of BLUJEPA have not been established for the treatment of uncomplicated urogenital gonorrhea in pediatric patients less than 12 years of age or weighing less than 45 kg.

8.5 Geriatric Use

Uncomplicated UTI

Of the total number of patients who received treatment with BLUJEPA in the uUTI studies (Trials 1 and 2), 226 (14%) were 65 to less than 75 years of age and 127 (8%) were 75 years of age and older [see Clinical Studies (14.1)]. No overall differences in safety or effectiveness of BLUJEPA were observed between patients 65 years of age and older and younger adult patients, but greater sensitivity of some older individuals cannot be ruled out.

BLUJEPA is known to be substantially excreted by the kidney, and the risk of adverse reactions to this drug may be greater in patients with impaired renal function [see Warnings and Precautions (5.1), Use in Specific Populations (8.6), Clinical Pharmacology (12.3)].

Uncomplicated Urogenital Gonorrhea

Trial 3 did not include sufficient numbers of subjects aged 65 years and older to determine whether they respond differently from younger subjects.

8.6 Renal Impairment

For Patients with uUTI or Uncomplicated Urogenital Gonorrhea

No dosage adjustment is required in patients with mild renal impairment (eGFR 60 to 89 mL/min) or moderate renal impairment (eGFR 30 to 59 mL/min).

Avoid use of BLUJEPA in patients with severe renal impairment or kidney failure (eGFR <30 mL/min), including those receiving dialysis, due to increased exposure to gepotidacin and the risk of QTc prolongation [see Warnings and Precautions (5.1), Clinical Pharmacology (12.3)].

Additional Recommendations for Patients with Uncomplicated Urogenital Gonorrhea

For patients with uncomplicated urogenital gonorrhea and moderate renal impairment (eGFR 30 to 59 mL/min), avoid use of BLUJEPA when additional risk factors for increased gepotidacin exposure are present [see Warnings and Precautions (5.1)].

8.7 Hepatic Impairment

For Patients with uUTI or Uncomplicated Urogenital Gonorrhea

No dosage adjustment is required in patients with mild or moderate hepatic impairment (Child‑Pugh Class A/B).

Avoid use of BLUJEPA in patients with severe hepatic impairment (Child‑Pugh Class C) due to increased exposure to gepotidacin and the risk of QTc prolongation [see Warnings and Precautions (5.1), Clinical Pharmacology (12.3)].

Additional Recommendations for Patients with Uncomplicated Urogenital Gonorrhea

For patients with uncomplicated urogenital gonorrhea and moderate hepatic impairment (Child-Pugh Class B), avoid use of BLUJEPA when additional risk factors for increased gepotidacin exposure are present [see Warnings and Precautions (5.1) and Clinical Pharmacology (12.3)].

10 OVERDOSAGE

There is a risk of QTc prolongation with overdosage. Intermittent hemodialysis is not likely to substantially remove BLUJEPA from the systemic circulation. Consider contacting the Poison Help line (1‑800‑222‑1222) or a medical toxicologist for additional overdose management recommendations.

11 DESCRIPTION

BLUJEPA tablets contain gepotidacin mesylate, a triazaacenaphthylene antibacterial that inhibits bacterial DNA gyrase and topoisomerase IV. The chemical name is (R)-2-((4-(((3,4-dihydro-2H-pyrano[2,3-c]pyridin-6-yl)methyl)amino)piperidin-1-yl)methyl)-1,2-dihydro-3H,8H-2a,5,8a-triazaacenaphthylene-3,8-dione methanesulfonate dihydrate. The molecular formula is C24H28N6O3●CH4O3S●2H2O and its molecular mass is 580.66. The structural formula is shown below.

*stereogenic center

Each BLUJEPA oral tablet contains gepotidacin 750 mg (equivalent to 910.7 mg of gepotidacin mesylate [anhydrous]). Inactive ingredients include colloidal silicon dioxide, croscarmellose sodium, magnesium stearate, microcrystalline cellulose, polyethylene glycol, polyvinyl alcohol, talc, titanium dioxide, and yellow iron oxide.

12 CLINICAL PHARMACOLOGY

12.1 Mechanism of Action

BLUJEPA is an antibacterial drug [see Microbiology (12.4)].

12.2 Pharmacodynamics

The 24-hour free‑drug AUC to minimum inhibitory concentration (MIC) ratio has been shown in animal infection and in vitro pharmacokinetic ‑pharmacodynamic (PK‑PD) models to be the PK‑PD index predictive of gepotidacin antibacterial efficacy.

Cardiac Electrophysiology

The effect of gepotidacin on the QTc interval was evaluated in a randomized, active (moxifloxacin 400 mg) and placebo‑controlled, double‑blind cross‑over trial in healthy subjects who received single intravenous (IV) infusions of gepotidacin over 2 hours. A dose- and concentration‑dependent QTc prolongation effect of gepotidacin was observed. The mean placebo‑corrected change from baseline heart rate values around Tmax were approximately 6 bpm at 1,000 mg IV (not an approved dosing regimen and route of administration) and approximately 10 bpm at 1,800 mg IV (not an approved dosing regimen and route of administration). The mean placebo‑corrected change from baseline QTcF values around Tmax were 12 msec at 1,000 mg IV and 22 msec at 1,800 mg IV [see Warnings and Precautions (5.1)]. The Cmax of gepotidacin following a single 1,000 mg IV dose (not an approved dosing regimen and route of administration) is approximately 1.2 times that of the Cmax at steady state for the 1,500 mg oral dose twice daily. The Cmax of gepotidacin following a single 1,800 mg IV dose (not an approved dosing regimen and route of administration) is approximately 1.2 times that of the Cmax after the second 3,000 mg oral dose given 12 hours after the first oral dose.

12.3 Pharmacokinetics

Pharmacokinetic Parameters

The pharmacokinetic properties of gepotidacin are summarized in Table 4 as mean (standard deviation [SD]) unless otherwise specified.

Table 4. Pharmacokinetic Parameters of Gepotidacin
Dosing Regimen | 1,500 mg Every 12 Hours over 5 Days | 2 Doses of 3,000 mg 12 Hours Apart
Exposure
Cmax (mcg/mL)a | 6.3 (1.0) | 11 (2.7)
AUC (mcg*hour/mL)a,b | 22.8 (4.8) | 75.9 (25.9)
Dose Proportionality | Approximately dose proportional from 1,500 to 3,000 mg
Accumulation | 40% and steady state was achieved by day 3
Absorption
Absolute Bioavailability | ~45%
Tmax (hours) | ~2.0
Effect of food (moderate fat meal)c | No clinically significant effect on PK
Distribution
Vss (L)a | 172.9 (42.5) | 188.0 (63.7)
Plasma Protein Binding | ~25 to ~41%
Elimination
Terminal Half-life (hours)a | 9.3 (1.3) | 9.4 (2.3)
Total Clearance (L/hour)a | 33.4 (6.7) | 34.8 (8.7)
Metabolism
Primary Pathway | Oxidative metabolism mediated by CYP3A4, producing several circulating metabolites
Major Metabolite (%) | M4 which is ~11% of circulating drug‑related materials
Excretion
Feces | ~52% (30% unchanged drug)
Urine | ~31% (20% unchanged drug; major route of elimination for absorbed gepotidacin)
a Pharmacokinetic parameters are presented at steady state in patients with uUTI and eGFR greater than or equal to 90 mL/min after oral administration of BLUJEPA 1,500 mg every 12 hours over 5 days, and in simulated results in adults with eGFR greater than or equal to 90 mL/min after oral administration of 2 doses of BLUJEPA (3,000 mg) taken 12 hours apart.
b AUC0-12 at steady state in patients with uUTI; simulated AUC0-24 on day 1 in simulated results with uncomplicated urogenital gonorrhea.
c Studies evaluating the effect on food were performed with standard and moderate fat meal. Clinical studies were not performed with a high fat meal (1,000 calories, 50% fat).

Specific Populations

Modelling and simulation analyses of gepotidacin showed that age, sex, and race have no clinically relevant effect on gepotidacin exposure. Body weight alone does not result in clinically significant effects on gepotidacin exposure [see Use in Specific Populations (8.4), (8.5)].

Patients with Renal Impairment: The pharmacokinetics of gepotidacin were evaluated in subjects with moderate renal impairment (eGFR 30 to 59 mL/min) and in subjects with severe renal impairment/end stage renal disease (ESRD) on intermittent hemodialysis and not on intermittent hemodialysis (eGFR <30 mL/min). Gepotidacin plasma Cmax and AUC in subjects with moderate renal impairment were 1.2-fold and 1.5-fold higher than matched healthy controls, respectively. Gepotidacin plasma Cmax and AUC in severe renal impairment/ESRD not on intermittent hemodialysis were 1.7-fold and 2.1‑fold higher than matched healthy controls, respectively. Gepotidacin plasma Cmax and AUC in ESRD subjects requiring intermittent hemodialysis were 2.3‑fold and 2.5-fold higher before intermittent hemodialysis than healthy matching subjects, respectively, and were 6.2‑fold and 4.2‑fold higher after intermittent hemodialysis than matched healthy controls, respectively [see Use in Specific Populations (8.6)].

Patients with Hepatic Impairment: Mild hepatic impairment did not have a clinically relevant effect on gepotidacin pharmacokinetics. Moderate hepatic impairment resulted in an approximately 1.2‑fold increase in gepotidacin plasma Cmax and AUC compared with normal hepatic function. In subjects with severe hepatic impairment compared with subjects with normal hepatic function, gepotidacin plasma exposure parameters (Cmax and AUC) were increased by approximately 1.9‑fold and 1.7‑fold, respectively [see Use in Specific Populations (8.7)].

Drug Interaction Studies

Clinical Drug Interaction Studies and Model Informed Approaches:

Effect of CYP3A4 Strong Inhibitors on the Pharmacokinetics of Gepotidacin: Concomitant administration of a strong inhibitor of CYP3A4 (itraconazole; 200 mg per day for 3 days), and a single 1,500 mg dose of BLUJEPA resulted in an increase in the maximum concentration (Cmax) of gepotidacin of approximately 1.4‑fold and area under the curve (AUC) of approximately 1.5‑fold [see Drug Interactions (7.1)].

Effect of CYP3A4 Strong Inducers on the Pharmacokinetics of Gepotidacin: Concomitant administration of BLUJEPA (single 1,500 mg dose) with a strong CYP3A4 inducer (rifampin; 600 mg once daily for 7 days) resulted in a decrease of 52% in gepotidacin plasma AUC(0-∞) [see Drug Interactions (7.1)].

Effect of BLUJEPA on Pharmacokinetics of Other Drugs: Concomitant administration of a single 0.5 mg dose of digoxin with two 3,000 mg doses of BLUJEPA (an in vitro P‑glycoprotein inhibitor), given 12 hours apart (not an approved dosage of BLUJEPA), resulted in a 1.5‑fold increase in the digoxin Cmax (at 3 hours post dose), a 1.1‑fold increase in the digoxin AUC(0-∞), and a delayed digoxin Tmax [see Drug Interactions (7.2)].

Concomitant administration of midazolam (2 mg single dose) with BLUJEPA (2 doses of 3,000 mg, given 12 hours apart; not an approved dosage of BLUJEPA) resulted in a 1.9‑fold increase in midazolam AUC(0-∞) [see Drug Interactions (7.2)].

Effect of Moderate CYP3A Inhibitors on the Pharmacokinetics of Gepotidacin: Concomitant administration of a moderate CYP3A inhibitor (fluconazole) and single 1,500 mg dose of BLUJEPA is predicted to increase gepotidacin Cmax by 1.3‑fold and AUC by 1.5‑fold [see Drug Interactions (7.1)].

Effect of Moderate CYP3A Inducers on the Pharmacokinetics of Gepotidacin: Concomitant administration of a moderate CYP3A inducer (efavirenz) and single 1,500 mg dose of BLUJEPA is predicted to decrease AUC and Cmax by 49% and 34%, respectively [see Drug Interactions (7.1)].

In Vitro Drug Interaction Studies: In vitro, gepotidacin was not an inducer of CYP1A2, 2B6 or 3A4. In vitro, gepotidacin is not a substrate of any of the hepatic organic anion transporting polypeptides (OATPs) 1B1, 1B3, and 2B1, organic anion transporters (OATs) OAT1, OAT2 and OAT3, organic cation transporters (OCTs) OCT2 and OCT3.

In Vitro Studies Where Drug Interaction Potential Was Not Further Evaluated Clinically: In vitro, gepotidacin inhibited multidrug and toxin extrusion (MATEs) MATE1 (IC50=16.6 µM), and MATE2‑K (IC50=6.9 μM). In vitro, gepotidacin is a substrate of breast cancer resistance protein (max flux rate ratio of 11.0).

12.4 Microbiology

Mechanism of Action

BLUJEPA is a triazaacenaphthylene antibacterial that inhibits Type II topoisomerases including bacterial topoisomerase II (DNA gyrase) and topoisomerase IV, thereby inhibiting DNA replication.

Gepotidacin has bactericidal activity against pathogens as determined by time‑kill studies. In vitro studies demonstrated a gepotidacin post‑antibiotic effect ranging from 1.8 to 2.2 hours for E. coli, 1 to >6.6 hours for K. pneumoniae, 1.4 to 3 hours for P. mirabilis, 1 to 2.6 hours for C. freundii, 2.7 to 4.3 hours for S. saprophyticus, 1.2 to 2.7 hours for E. faecalis, and 0.7 to 1 hour for N. gonorrhoeae at 5 times the MIC.

Resistance

Although no clear mechanisms of resistance have been identified for gepotidacin, potential mechanisms that may impact gepotidacin activity are gepotidacin‑specific alterations of DNA gyrase (gyrA, gyrB) and/or topoisomerase IV (parC, parE) gene targets, plasmid‑mediated quinolone resistance genes (especially qnr), and efflux. The following amino acids may be important for gepotidacin activity GyrA P35, V44, D82, A175, GyrB D426, P445 and ParC D79 (based on E. coli numbering) as shown through studies with isogenic mutants in E. coli and K. pneumoniae. The amino acids GyrA D90, A92 and ParC D86 (based on N. gonorrhoeae numbering) as shown through studies with isogenic mutants in N. gonorrhoeae may also be important. A single target‑specific mutation may not significantly impact gepotidacin activity. In studies of certain amino acid substitutions in GyrA and ParC of E.coli and N. gonorrhoeae, a direct relationship between gepotidacin and fluoroquinolone susceptibility was not established. However, in a study of isogenic N. gonorrhoeae strains with mutations in GyrA S91F, A92T, D95G, and ParC D86N, resistance to both gepotidacin and ciprofloxacin was observed. The clinical significance of these findings is unknown. Gepotidacin activity against E. coli, K. pneumoniae, and N. gonorrhoeae is unrelated to beta‑lactam resistance mechanisms.

The frequency of resistance development to gepotidacin due to spontaneous mutations in the gram‑negative pathogens and gram‑positive uropathogens tested in vitro at 10 times MIC ranged from 10^-9 to 10^-10.

Target‑specific cross‑resistance with other classes of antibacterial drugs has not been identified; therefore, isolates resistant to other drugs may be susceptible to gepotidacin. However, isolates of Enterobacterales with ≥4‑fold increases in gepotidacin MIC have been identified in vitro and in clinical studies. Using an unapproved single dose of ≤3,000 mg of gepotidacin, three microbiological failures were reported among patients from the Phase 2 clinical study with N. gonorrhoeae isolates with a baseline MIC of 1 mcg/mL. Two of these isolates at the end of treatment, had mutations in GyrA and ParC known to be important for gepotidacin binding to the target (ParC D86N, GyrA A92T), and resistance to gepotidacin (MIC increased ≥32‑fold). Using 3,000 mg of gepotidacin followed by a second 3,000 mg dose taken approximately 12 hours later, no N. gonorrhoeae isolates with gepotidacin MIC values >2 mcg/mL were observed, including for pre‑treatment isolates with a ParC D86N mutation.

During clinical studies, gepotidacin demonstrated activity against some isolates of the following multilocus sequence typing (MLST) for E. coli: ST10, ST131, ST1193, ST69, ST95 and ST73. In vitro activity was also demonstrated against the following N. gonorrhoeae MLSTs: ST11422, ST11706, ST1580, ST1583, ST7363, ST7822 and ST9362.

Interaction with Other Antimicrobials

In in vitro studies, no antagonism against Enterobacterales or gram‑positive isolates was observed for gepotidacin in combination with multiple antibacterial drugs, including fluoroquinolones, sulfonamides, cephalosporins, macrolides, tetracyclines, aminoglycosides, glycopeptides, carbapenems, nitrofurans, monobactams, and oxazolidinones, or for N. gonorrhoeae for gepotidacin in combination with fluoroquinolones, cephalosporins, macrolides, tetracyclines, aminoglycosides, pleuromutilins, and aminocyclitols.

Antimicrobial Activity

Gepotidacin has been shown to be active against most isolates of the following microorganisms, both in vitro and in clinical infections [see Indications and Usage (1)]:

Uncomplicated UTI:

Aerobic bacteria

Gram‑positive bacteria

Enterococcus faecalis

Staphylococcus saprophyticus

Gram‑negative bacteria

Citrobacter freundii complex

Escherichia coli

Klebsiella pneumoniae

Uncomplicated Urogenital Gonorrhea:

Aerobic bacteria

Gram‑negative bacteria

Neisseria gonorrhoeae

The following in vitro data are available, but their clinical significance is unknown. At least 90 percent of the following bacteria exhibit an in vitro minimum inhibitory concentration (MIC) less than or equal to the susceptible breakpoint for gepotidacin against isolates of similar genus or organism group. However, the efficacy of gepotidacin in treating clinical infections caused by these bacteria has not been established in adequate and well‑controlled clinical trials.

Aerobic bacteria

Gram‑negative bacteria

Citrobacter koseri

Klebsiella aerogenes

Klebsiella oxytoca/Raoltella ornithinolytica

Morganella morganii

Proteus mirabilis

Providencia rettgeri

Susceptibility Test Methods

For specific information regarding susceptibility test interpretive criteria and associated test methods and quality control standards recognized by FDA for this drug, please see: https://www.fda.gov/STIC.

13 NONCLINICAL TOXICOLOGY

13.1 Carcinogenesis, Mutagenesis, Impairment of Fertility

Carcinogenesis

Long term carcinogenicity studies have not been conducted with gepotidacin.

Mutagenesis

Gepotidacin was positive in an in vitro micronucleus test in human peripheral blood lymphocytes and in an L5178Y mouse lymphoma assay, consistent with the known in vitro clastogenic effects of topoisomerase inhibitors in in vitro mammalian cell assays. Gepotidacin was negative in an in vivo micronucleus test or Comet assay in rat. Based on an overall weight of evidence, gepotidacin is unlikely to be genotoxic.

Impairment of Fertility

In animal studies with gepotidacin, there were no adverse effects on fertility in male and female rats treated for approximately 3 weeks at approximately 2 times the exposure at the MRHD (AUC extrapolated from rats orally administered the same dose for up to 4 weeks). There were no effects on spermatogenesis in rats and dogs at approximately 2 and 3 times the exposure at MRHD, respectively, when treated for up to 13 weeks.

14 CLINICAL STUDIES

14.1 Uncomplicated Urinary Tract Infections

A total of 3,136 female patients with uncomplicated urinary tract infections (uUTI) were randomized in 2 multicenter, parallel‑group, double‑blind, double‑dummy, non‑inferiority (NI) trials (Trial 1 [NCT04020341] and Trial 2 [NCT04187144]). Both trials compared BLUJEPA 1,500 mg (administered orally twice daily with food for 5 days) to nitrofurantoin 100 mg (administered orally twice daily for 5 days).

Patients entered the trials with at least 2 symptoms consistent with uUTI (dysuria, frequency, urgency, or lower abdominal pain) and with evidence of urinary nitrite or pyuria. Patients with any medical condition or presentation suggestive of a complicated UTI, or an upper UTI (e.g., pyelonephritis, urosepsis) were excluded.

Efficacy was assessed as a composite of clinical cure and microbiological response at the Test‑of‑Cure (TOC) Visit (study day 10 to 13) in the microbiological ITT nitrofurantoin‑susceptible (micro‑ITTS) population, which included all patients who received at least 1 dose of study medication, had at least 1 baseline qualifying uropathogen (≥10^5 colony‑forming units [CFU]/mL), and excluded patients with organisms not susceptible to nitrofurantoin. Clinical cure was defined as resolution of all signs and symptoms of acute cystitis present at baseline and no new signs and symptoms without the patient receiving other systemic antimicrobials.

Microbiological response was defined as having all qualifying uropathogens found at baseline at ≥10^5 CFU/mL reduced to <10^3 CFU/mL without the patient receiving other systemic antimicrobials.

Both trials demonstrated non‑inferiority of BLUJEPA to nitrofurantoin for composite response (Table 5).

In Trial 1, the micro‑ITTS population consisted of 634 female patients with uUTI (n = 336 BLUJEPA; n = 298 nitrofurantoin). The median age of patients was 54 years, 57% were >50 years of age, 84% were White, 40% had a history of recurrent infection. The U.S. enrolled the greatest percentage of patients (39%). Patient demographic and baseline characteristics were generally balanced between treatment groups [see Adverse Reactions (6.1)].

In Trial 2, the micro‑ITTS population consisted of 567 female patients with uUTI (n = 292 BLUJEPA; n = 275 nitrofurantoin). The median age of patients was 51 years, 52% were >50 years of age, 85% were White, 41% had history of recurrent infection. The majority of patients (67%) were enrolled from the United States. Patient demographic and baseline characteristics were generally balanced between treatment groups [see Adverse Reactions (6.1)].

Table 5 summarizes the composite response, clinical cure, and microbiological response rates at the TOC visit for Trials 1 and 2 in the micro‑ITTS population.

Table 5. Composite Response, Clinical Cure, and Microbiological Response Rates at the Test-of-Cure Visit (Micro-ITTS Population)
Study Endpoint | BLUJEPA; n/N (%) | Nitrofurantoin; n/N (%) | Treatment Difference; (95% CI)b
Trial 1
Composite responsea | 174/336 (51.8) | 140/298 (47.0) | 5.3 (-2.4, 13.0)
Clinical cure | 224/336 (66.7) | 196/298 (65.8) | 1.5 (-5.8, 8.8)
Microbiological response | 244/336 (72.6) | 199/298 (66.8) | 6.0 (-1.2, 13.1)
Trial 2
Composite responsea | 172/292 (58.9) | 121/275 (44.0) | 14.4 (6.4, 22.4)
Clinical cure | 199/292 (68.2) | 175/275 (63.6) | 4.3 (-3.4, 12.0)
Microbiological response | 213/292 (72.9) | 158/275 (57.5) | 15.5 (7.9, 23.1)
micro-ITTS = microbiological Intent to Treat nitrofurantoin-susceptible; CI = confidence interval.
a BLUJEPA was non-inferior to nitrofurantoin in both studies. The determination of Trial 1 non‑inferiority was based on a planned interim analysis of 607 subjects in micro-ITTS population. The determination of Trial 2 non‑inferiority was based on a planned interim analysis of 541 subjects in micro-ITTS population.
b Treatment difference (BLUJEPA – nitrofurantoin) calculated using Miettinen and Nurminen Summary Score method adjusting for age group and recurrent/non-recurrent infection status combinations.

Table 6 summarizes the composite response rates at the TOC Visit for the most common baseline uropathogens across both trials in the micro-ITTS population.

Table 6. Composite Response Rates at the Test-of-Cure Visit by Baseline Uropathogen (Trial 1 and Trial 2 Pooled; Micro-ITTS Population)a
Pathogenb | BLUJEPAa; n/N (%) | Nitrofurantoina; n/N (%)
Escherichia coli | 312/566 (55.1) | 234/520 (45.0)
Klebsiella pneumoniae | 6/14 (42.9) | 6/16 (37.5)
Staphylococcus saprophyticus | 9/15 (60.0) | 11/14 (78.6)
Enterococcus faecalis | 8/14 (57.1) | 2/7 (28.6)
Citrobacter freundii complex | 8/12 (66.7) | 2/5 (40.0)
micro‑ITTS = microbiological Intent to Treat nitrofurantoin-susceptible
a A patient is counted once under a uropathogen category if multiple qualifying uropathogens within that category are isolated at baseline for the patient.
b Patients may have been infected with 1 to 2 uropathogens at baseline.

14.2 Uncomplicated Urogenital Gonorrhea

A total of 628 patients with suspected uncomplicated urogenital gonorrhea due to Neisseria gonorrhoeae were randomized in an open‑label, active‑controlled, multicenter, multinational trial (Trial 3; NCT04010539). Patients were randomized 1:1 to receive either BLUJEPA (3,000 mg taken orally followed by a second dose of 3,000 mg approximately 12 hours later), or a combination of a single intramuscular 500 mg dose of ceftriaxone and single 1 g oral dose of azithromycin.

Patients were eligible for enrollment if they were ≥12 years old and >45 kg. Patients with confirmed or suspected complicated or disseminated gonorrhea were excluded from the study. The microbiological intent‑to‑treat (micro‑ITT) population, which included patients who had urogenital N. gonorrhoeae isolated at baseline and who were not infected with a strain that was nonsusceptible to ceftriaxone at baseline, consisted of 406 patients (202 for BLUJEPA and 204 for ceftriaxone and azithromycin). The demographic and baseline characteristics in the micro‑ITT population were comparable between treatment groups. In total, 92% were male; 74% White, 15% Black, 6% Asian, 17% Hispanic or Latino; the mean age was 33 years (range: 17 to 64); the mean weight was 76 kg (range: 48 to 120 kg). The primary efficacy endpoint was microbiological success as determined by confirmed bacterial eradication of N. gonorrhoeae at the urogenital body site at the test of cure (TOC) visit (Day 4 to 8) without receipt of other systemic antimicrobials and was assessed in the micro‑ITT population.

Table 7 shows the primary endpoint of the microbiological success rates at the urogenital site at TOC in the micro‑ITT population. Trial 3 demonstrated non‑inferiority of BLUJEPA to the combination of ceftriaxone and azithromycin.

Table 7. Microbiological Success Rates at the Urogenital Site at TOC, Micro-ITT Population (Trial 3)
 | BLUJEPA; n/N (%) | Ceftriaxone and Azithromycin; n/N (%) | Treatment Difference; (95% CI)a
Microbiological success | 187/202 (92.6) | 186/204 (91.2) | -0.1 (-5.6, 5.5)
Microbiological failure | 15/202 (7.4) | 18/204 (8.8)
Bacterial persistence by culture | 0 | 0
Unable to determineb | 15/202 (7.4) | 18/204 (8.8)
TOC = Test of Cure; micro‑ITT = microbiological Intent to Treat; CI=confidence interval; n = number of patients in subcategory; N = number of patients in the specified population
a Calculated using Miettinen and Nurminen Summary Score method adjusting for sex and sexual orientation (female, men who have sex with men, or men who have sex with women) for the BLUJEPA – (ceftriaxone and azithromycin) treatment difference.
b Unable to determine outcomes were due to missing data, culture processed beyond 24 hours, TOC out of window, or use of another systemic antimicrobial prior to the TOC visit

16 HOW SUPPLIED/STORAGE AND HANDLING

BLUJEPA tablets are supplied as yellow, film-coated, capsule-shaped tablets debossed with “GS GU3” on one side and plain on the other side, containing 750 mg of gepotidacin.

Bottle of 8 tablets (NDC 0173-0922-38).

Bottle of 20 tablets (NDC 0173-0922-45).

Store at 20°C to 25°C (68°F to 77°F); excursions permitted between 15°C and 30°C (59°F and 86°F). [See USP Controlled Room Temperature].

17 PATIENT COUNSELING INFORMATION

Advise the patient to read the FDA-approved patient labeling (Medication Guide).

Important Administration Instructions

Counsel patients to take BLUJEPA after a meal to reduce the possibility of gastrointestinal intolerance [see Dosage and Administration (2.3)].

Prolongation of the QTc Interval

Counsel patients to inform their healthcare provider of any personal or family history of QTc prolongation or proarrhythmic conditions such as hypokalemia, bradycardia, or recent myocardial ischemia, or if they are taking any antiarrhythmic agents. Advise patients to notify their healthcare providers if they have any symptoms of prolongation of the QTc interval, including prolonged heart palpitations or a loss of consciousness [see Warnings and Precautions (5.1)].

Acetylcholinesterase Inhibition

Counsel patients that BLUJEPA can cause dysarthria and other symptoms such as syncope, presyncope, muscle spasms, diarrhea, nausea, vomiting, abdominal pain, hypersalivation, and hyperhidrosis. Advise patients to inform their healthcare provider if they experience these symptoms or if they have an underlying medical condition that may be exacerbated by acetylcholinesterase inhibition or are planning to receive anesthesia where they may receive neuromuscular blocking agents, or if they are receiving other acetylcholinesterase inhibitors, or systemic anticholinergic medications [see Warnings and Precautions (5.2), Drug Interactions (7.3)].

Hypersensitivity Reactions

Advise patients that hypersensitivity reactions, including anaphylaxis, could occur and require immediate treatment. Advise patients to inform their healthcare provider about any previous hypersensitivity reactions to BLUJEPA [see Warnings and Precautions (5.3)].

Diarrhea

Counsel patients that diarrhea is a common problem caused by antibacterials, including BLUJEPA. Most reported cases of diarrhea with BLUJEPA were mild to moderate in severity. Diarrhea may occur early in treatment and usually ends when treatment with the antibacterial is discontinued. In most cases, the diarrhea resolved without treatment [see Warnings and Precautions (5.2), Adverse Reactions (6.1)].

Sometimes potentially serious diarrhea with frequent watery or bloody diarrhea may occur and may be a sign of a more serious intestinal infection. If severe watery or bloody diarrhea develops, patients should contact their healthcare provider [see Warnings and Precautions (5.4)].

Antibacterial Resistance

Patients should be counseled that antibacterial drugs, including BLUJEPA, should only be used to treat bacterial infections. They do not treat viral infections (e.g., the common cold). When BLUJEPA is prescribed to treat a bacterial infection, patients should be told that although it is common to feel better early in the course of therapy, the medication should be taken exactly as directed. Skipping doses or not completing the full course of therapy may: (1) decrease the effectiveness of the immediate treatment and (2) increase the likelihood that bacteria will develop resistance and will not be treatable by BLUJEPA or other antibacterial drugs in the future [see Warnings and Precautions (5.5)].

Drug Interactions

Advise patients of the potential interactions other medications may have with BLUJEPA or the effect BLUJEPA may have on other medications, as these may result in decreased effectiveness or increased toxicities of either BLUJEPA or the other medications. Patients should alert their healthcare provider if they are currently taking any medications, including herbal nutritional supplements, or are prescribed new medications during treatment with BLUJEPA [see Warnings and Precautions (5.1), Drug Interactions (7), Clinical Pharmacology (12.3)].

Pregnancy

Advise patients who are exposed to BLUJEPA during pregnancy to contact GlaxoSmithKline at 1‑888‑825‑5249 [see Use in Specific Populations (8.1)].

Manufactured for:

GlaxoSmithKline

Durham, NC 27701

Trademarks are owned by or licensed to the GSK group of companies.

©2026 GSK group of companies or its licensor.

BLJ:3PI

MEDICATION GUIDE

BLUJEPA (blu – JEP – ah)

(gepotidacin)

tablets, for oral use

What is the most important information I should know about BLUJEPA?

BLUJEPA, an antibiotic, can cause serious side effects, including:

- changes in electrical activity of your heart called QTc prolongation. BLUJEPA can cause QTc prolongation (also called prolonged QTc interval) that can lead to serious heart rhythm problems, including Torsade de Pointes. There may be changes in your heartbeat (a fast or irregular heartbeat).
  Before starting BLUJEPA, tell your healthcare provider if you:
  - or anyone in your family has ever had a heart rhythm problem (problem with heart rate or heartbeat) or QTc prolongation.
  - are taking any medicines to treat heart rhythm problems. Using these medicines with BLUJEPA may cause serious side effects. If you are not sure, ask your healthcare provider.
  - are taking medicines called moderate or strong CYP3A4 inhibitors. Using these medicines with BLUJEPA may cause serious side effects. If you are not sure, ask your healthcare provider.

Tell your healthcare provider right away if you have any of the following symptoms:

○fast, pounding, or uneven heartbeat
○feeling dizzy
○you lose consciousness (pass out)

○feeling lightheaded
○feeling faint

- an increase of a certain chemical in your nervous system (cholinergic effects). BLUJEPA can cause an increase of a certain chemical in your nervous system, which may cause the following symptoms:

○diarrhea
○vomiting
○fainting
○trouble saying words clearly
○muscle spasms

○nausea
○more saliva in the mouth
○more sweating
○stomach pain

Call your healthcare provider right away if you have trouble saying words clearly, have shortness of breath, or if you faint. These symptoms may be cholinergic effects of BLUJEPA.

The increased chemical in your nervous system can also be connected to other symptoms. Call your healthcare provider right away if you have any of these additional symptoms.

○irregular heartbeat (heart block)
○slow heartbeat (bradycardia)
○seizures

○fainting
○chest tightness causing difficulty breathing

- allergic reactions. Allergic reactions can happen in people who take BLUJEPA including a severe allergic reaction called anaphylaxis. Stop taking BLUJEPA and get medical help right away if you have any symptoms of a severe allergic reaction, including:

○hives
○feeling faint or dizzy

○rash
○swelling of your lips, tongue, or throat

- diarrhea. Diarrhea is a common side effect caused by antibiotics including BLUJEPA. The diarrhea may happen at the beginning of your treatment with BLUJEPA and usually stops after the antibiotic is stopped. In most cases the diarrhea will go away without treatment. In some cases, diarrhea may be caused by Clostridioides difficile infection (CDI). CDI is a severe infection of the intestines (bowels) that can happen up to 2 months after finishing treatment with antibiotic medicines, including BLUJEPA. CDI can be life-threatening and can lead to death. Do not take medicines to treat diarrhea without checking first with your healthcare provider. Call your healthcare provider right away if you have the following symptoms:

○stomach cramps
○fever
○watery diarrhea

○diarrhea that does not go away
○bloody stools

What is BLUJEPA?

BLUJEPA is an antibiotic used to treat:

- Women and girls 12 years of age and older weighing at least 88 pounds who have an infection of the bladder (known as an uncomplicated urinary tract infection [uUTI]) caused by certain types of bacteria.
- Adults and children 12 years of age and older weighing at least 99 pounds who have very few or no other medicine choices to treat a sexually transmitted disease called uncomplicated urogenital gonorrhea (gonorrhea) caused by a certain type of bacteria.
- It is not known if BLUJEPA is safe and effective for the treatment of uUTI in children under 12 years of age or weighing less than 88 pounds.
- It is not known if BLUJEPA is safe and effective for the treatment of gonorrhea in children under 12 years of age or weighing less than 99 pounds.

Do not take BLUJEPA if:

you have had a severe allergic reaction to BLUJEPA. See the end of this Medication Guide for a complete list of ingredients in BLUJEPA.

Before taking BLUJEPA, tell your healthcare provider about all of your medical conditions, including if you:

- have heart rhythm problems. See “What is the most important information I should know about BLUJEPA?”
- have a slow heartbeat (bradycardia).
- have recently had a heart attack.
- have low potassium in your blood (hypokalemia).
- are planning to have a medical or surgical procedure that puts you to sleep (general anesthesia) that will use a type of medicine given through your veins (I.V.) that relaxes your muscles.
- have liver problems.
- have kidney problems, kidney failure, or are on dialysis.
- are pregnant or plan to become pregnant. It is not known if BLUJEPA will harm your unborn baby.

Tell your healthcare provider if you become pregnant or think you are pregnant during your treatment with BLUJEPA.

- Pregnancy Exposure Registry: There is a pregnancy exposure registry for women who are exposed to BLUJEPA during pregnancy. The purpose of this registry is to check the health of you and your baby. If you are pregnant or become pregnant during your treatment with BLUJEPA, talk to your healthcare provider about registering with GlaxoSmithKline. You can register by calling GlaxoSmithKline at 1‑888‑825‑5249.
- are breastfeeding or plan to breastfeed. It is not known if BLUJEPA passes into breast milk. Talk to your healthcare provider about the best way to feed your baby during your treatment with BLUJEPA.

Tell your healthcare provider about all the medicines you take, including prescription and over-the-counter medicines, vitamins, and herbal supplements. BLUJEPA and other medicines may affect each other causing side effects.

Especially tell your healthcare provider if you take medicines to treat heart rhythm problems.

Ask your healthcare provider or pharmacist, if you are not sure if you are taking any of these medicines. Know the medicines you take. Keep a list of them to show to your healthcare provider and pharmacist when you get a new medicine.

How should I take BLUJEPA?

- Take BLUJEPA exactly as your healthcare provider tells you to take it. Check with your healthcare provider if you are not sure.
- The dose of BLUJEPA for the treatment of uUTI, is 2 tablets by mouth, 2 times each day (about 12 hours apart), for 5 days.
- The dose of BLUJEPA for the treatment of gonorrhea is 4 tablets taken by mouth followed by a second dose of 4 tablets about 12 hours later.
- Take BLUJEPA after a meal to decrease the chance of stomach upset.
- For the treatment of uUTI:
○If you miss a dose, take it as soon as possible, then continue your treatment as before. Do not take 2 doses to make up for a missed dose.
- For the treatment of gonorrhea:
○If you miss a dose, take it as soon as possible.
- If you take too much BLUJEPA, call the Poison Help line at 1‑800‑222‑1222 or go to the nearest hospital emergency room right away.
- Take the full course of treatment with BLUJEPA. Do not stop taking BLUJEPA during your treatment unless your healthcare provider tells you to, even if you are feeling better. If you do not complete your full course of treatment, the infection may come back.

What are the possible side effects of BLUJEPA?

BLUJEPA can cause serious side effects including:

- See “What is the most important information I should know about BLUJEPA?”

The most common side effects of BLUJEPA in people with uUTI include:

○diarrhea
○nausea
○stomach pain
○gas
○headache

○soft stools
○dizziness
○vomiting
○yeast infections

The most common side effects of BLUJEPA in people with gonorrhea include:

○diarrhea
○nausea
○stomach pain
○vomiting
○gas

○dizziness
○soft stools
○headache
○feeling tired
○excessive sweating

These are not all the possible side effects of BLUJEPA. Call your doctor for medical advice about side effects. You may report side effects to FDA at 1-800-FDA-1088.

How should I store BLUJEPA?

- Store BLUJEPA tablets at room temperature between 68°F to 77°F (20°C to 25°C).

Keep BLUJEPA and all medicines out of the reach of children.

General information about the safe and effective use of BLUJEPA.

Medicines are sometimes prescribed for purposes other than those listed in a Medication Guide. Do not use BLUJEPA for a condition for which it was not prescribed. Do not give BLUJEPA to other people, even if they have the same symptoms that you have. It may harm them.

You can ask your pharmacist or healthcare provider for information about BLUJEPA that is written for health professionals.

What are the ingredients in BLUJEPA?

Active ingredient: gepotidacin mesylate

Inactive ingredients: colloidal silicon dioxide, croscarmellose sodium, magnesium stearate, microcrystalline cellulose, polyethylene glycol, polyvinyl alcohol, talc, titanium dioxide and yellow iron oxide.

Manufactured for:

For more information, call 1‑888‑825‑5249 or go to www.gsk.com.

Trademarks are owned by or licensed to the GSK group of companies.

GlaxoSmithKline, Durham, NC 27701

©2025 GSK group of companies or its licensor.

BLJ:2MG

This Medication Guide has been approved by the U.S. Food and Drug Administration. Revised: 12/2025

PACKAGE LABEL

PRINCICPAL DISPLAY PANEL

NDC 0173-0922-45

BLUJEPA

(gepotidacin)

tablets

750 mg

Rx only

Dispense the accompanying Medication Guide to each patient

20 tablets

GSK

Each tablet contains gepotidacin 750 mg (equivalent to 910.7 mg of gepotidacin mesylate [anhydrous]).

Store at 20°C to 25°C (68°F to 77°F); excursions permitted between 15°C to 30°C (59°F to 86°F). [See USP Controlled Room Temperature].

Keep out of reach of children.

Do not accept if safety seal under cap is missing or broken.

Recommended Dosage: see Prescribing Information.

Trademarks owned or licensed by GSK.

Mft. For: GSK, Durham, NC 27701

Scan for product information or visit epi-pla.org

Made in Belgium

©2025 GSK or licensor. Rev. 03/25

2000017942